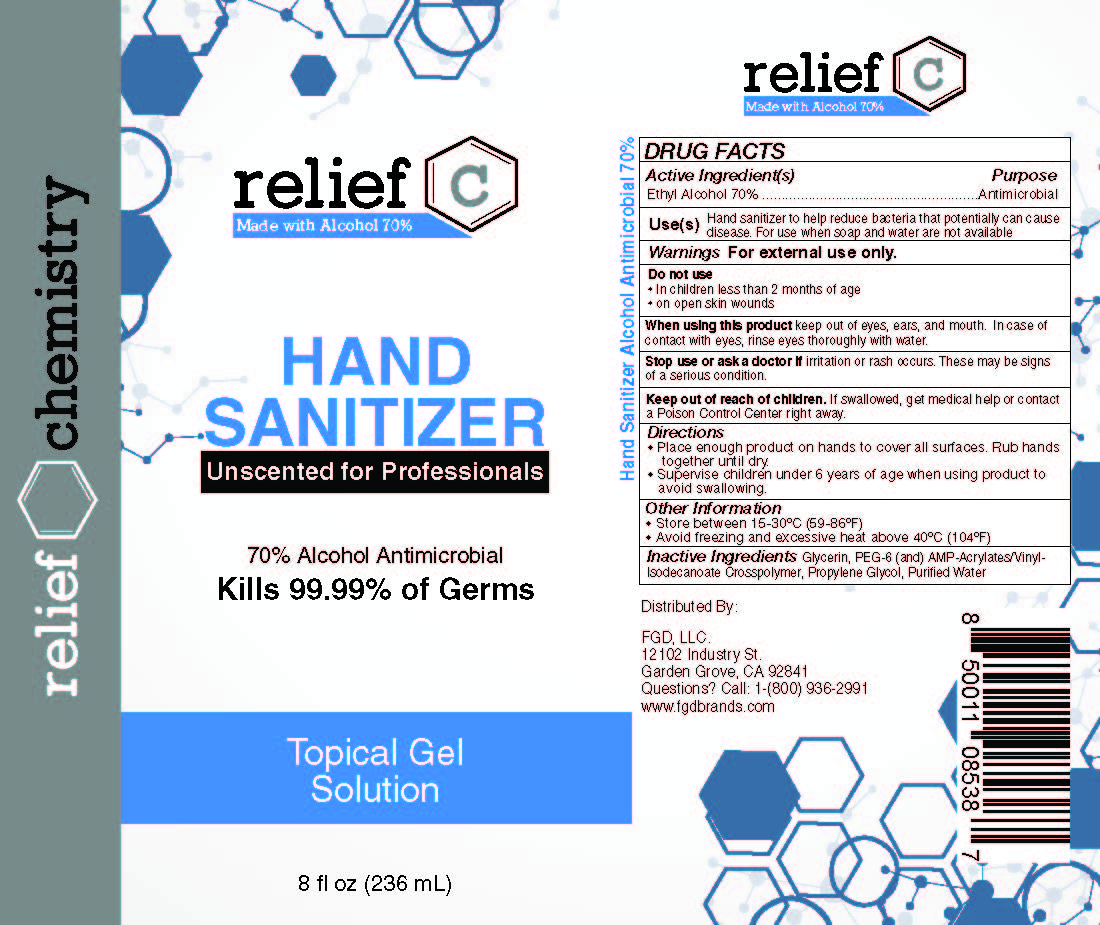 DRUG LABEL: Relief C Hand Sanitizer Unscented for Professionals
NDC: 73787-119 | Form: GEL
Manufacturer: FGD, LLC
Category: otc | Type: HUMAN OTC DRUG LABEL
Date: 20210106

ACTIVE INGREDIENTS: ALCOHOL 70 mL/100 mL
INACTIVE INGREDIENTS: ACRYLATES/VINYL ISODECANOATE CROSSPOLYMER (10000 MPA.S NEUTRALIZED AT 0.5%); WATER; PROPYLENE GLYCOL; GLYCERIN; POLYETHYLENE GLYCOL 300

Relief C Hand Sanitizer Unscented for Professionals 8 oz rapidgel

Active ingredient

Ethyl Alcohol 70%

Purpose

Antimicrobial

Uses

Hand sanitizer to help reduce bacteria that can potentially cause disease. For use when soap and water are not available

Warnings

For external use only. Flammable. Keep away from heat or flame.

DO NOT USE

- on children less than 2 months of age
- on open skin wounds

WHEN USING

keep out of eyes, ears, and mouth. In case of contact with eyes, rinse eyes thoroughly with water.

STOP USE

if irritation or rash occurs. These may be signs of a serious condition.

KEEP OUT OF REACH OF CHILDREN

If swallowed, get medical help or contact a Poison Control Center right away.

Directions

- Place enough product on hands to cover all surfaces. Rub hands together until dry.
- Supervise children under 6 years of age when using hit produce to avoid swallowing.

OTHER SAFETY INFORMATION

- Store between 15-30oC (59-86oF)
- Avoid freezing and excessive heat 40oC (104oF)

Inactive ingredients

Glycerin, PEG-6 (and) AMP-Acrylate/vinyl-Isodecanoate Crosspolymer, Propylene-glycol, Purified Water